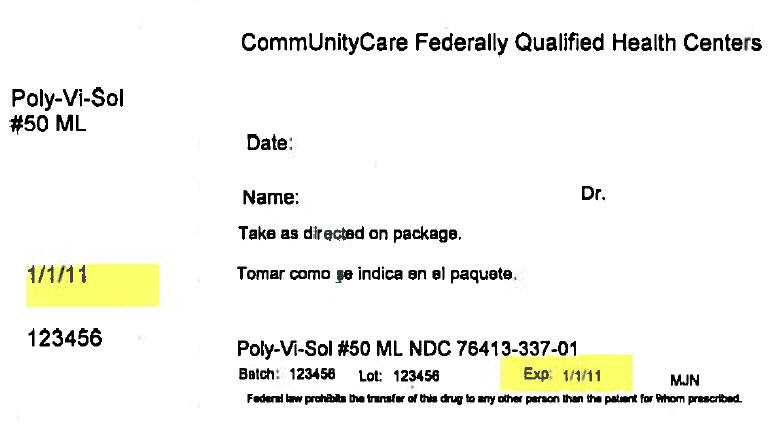 DRUG LABEL: Poly-Vi-Sol
NDC: 76413-337 | Form: LIQUID
Manufacturer: Central Texas Community Health Centers
Category: other | Type: DIETARY SUPPLEMENT
Date: 20171020

ACTIVE INGREDIENTS: Vitamin A 750 [iU]/1 mL; Vitamin D 400 [iU]/1 mL; .ALPHA.-TOCOPHEROL 5 [iU]/1 mL; THIAMINE 0.5 mg/1 mL; Riboflavin 0.6 mg/1 mL; Niacin 8 mg/1 mL; PYRIDOXINE 0.4 mg/1 mL; CYANOCOBALAMIN 2 ug/1 mL
INACTIVE INGREDIENTS: glycerin; water; polysorbate 80; sulfuric acid

Enfamil® Poly-Vi-Sol

HEALTH CLAIM

Liquid multivitamin supplement

Last updated: Tuesday, November 18, 2014

Indication

Multivitamin supplementation for infants and children.

Enfamil Poly-Vi-Sol Liquid Multivitamin Supplement is recommended for infants around 4–6 months of age who are transitioning to solid foods.

• Rationale and Special Characteristics

- Enfamil Poly-Vi-Sol Liquid Multivitamin Supplement has 9 important vitamins in a convenient daily dose. It is an excellent supplement for a child when transitioning to solid foods, during growth spurts and for the picky eater. Enfamil Poly-Vi-Sol Liquid Multivitamin Supplement (without iron) is recommended for children who have sufficient iron in their diet or the possibility of too much.
  The American Academy of Pediatrics (AAP) recommends 400 IU of supplemental vitamin D per day beginning in the first days of life for all breastfed and partially breastfed infants who do not receive at least 1 L of infant formula per day^1.
  Enfamil Poly-Vi-Sol Liquid Multivitamin Supplement is does not contain ingredients derived from the most common food allergies: milk, eggs, peanuts, tree nuts, fish, shellfish, soy or wheat.
  Refrigeration is not required.

• Nutrients

 | Per 1 mL | % DV Infants | % DV Children under 4 years
Vitamin A, IU | 750 | 50 | 30
Vitamin D, IU | 400 | 100 | 100
Vitamin E, IU | 5 | 100 | 50
Vitamin C, mg | 35 | 100 | 88
Thiamin, mg | 0.5 | 100 | 71
Riboflavin, mg | 0.6 | 100 | 75
Niacin, mg | 8 | 100 | 89
Vitamin B6, mg | 0.4 | 100 | 57
Vitamin B12, mcg | 2 | 100 | 67
o Note: Enfamil Poly-Vi-Sol Liquid Multivitamin Supplement does not include folic acid

• Osmolality

- When added to 2 fl oz of infant formula or breast milk, 1 mL of Enfamil® Poly-Vi-Sol® increases the osmolality by +160 mOsmol /kg water^2. If the resulting osmolality is higher than desired for a particular baby, an option is to add 0.5 mL of the supplement to the feeding twice per day.

• Product Form

- Enfamil Poly-Vi-Sol Liquid Multivitamin Supplement is available as drops in 50 mL bottles.

Item #: 040265
Description: With Dropper
Unit Size: 50 mL
Cal./Unit: N/A
Prod. Yield / Unit (fl oz): N/A
Case: 12 bottles per case
Reimbursement Code: 00087-040203

Usual Daily Dose

Drops: 1.0 mL

• Composition

- Ingredients: Glycerin, water, ascorbic acid, vitamin E succinate, niacinamide, polysorbate 80, ferrous sulfate (stabilizer for vitamin B12), caramel color, vitamin A palmitate, thiamin hydrochloride, riboflavin-5-phosphate sodium, vitamin D3, vitamin B6 hydrochloride, natural and artificial flavor, sulfuric acid (antioxidant for iron), vitamin B12, sulfites.

• Administration

- Drops: Now includes an easy-to-use syringe. The syringe is marked with 0.25 mL, 0.5 mL, 0.75 mL and 1.0 mL dose lines. To administer directly, place the syringe in the child's mouth with the tip against the inside of the cheek. A firm pressure on the syringe bulb will deliver the proper dose. A slight excess will remain in the syringe. If preferred, the drops may be slowly mixed with formula, juice, cereal or other food and fed within 1 hour.

• Storage

- Store at room temperature. Refrigeration is not required, but will not harm the drops.

• Precautions

- As with all vitamin products, parents should be cautioned against excessive dosage. The bottle should be kept out of the reach of children.

• References

○ 1. Wagner CL, Greer FR, and the American Academy of Pediatrics Section on Breastfeeding and Committee on Nutrition. Prevention of rickets and vitamin D deficiency in infants, children, and adolescents. Pediatrics. 2008;122:1142-1152.
2. Testing was conducted in September 2009 by Mead Johnson Nutrition, Quality Control.

HEALTH CLAIM

Above information found at:

Enfamil Poly-Vi-Sol. On Mead-Johnson Nutrition website. Available at: https://www.meadjohnson.com/pediatrics/us-en/product-information/products/vitamins/enfamil-poly-vi-sol-drops#references. Accessed 9/7/17.

PRINCIPAL DISPLAY PANEL - 50 ML Bottle Box Label

CommUnityCare Federally Qualified Health Centers

Poly-Vi-Sol
#50 ML

Date:

Name:
Dr.

Take as directed on package.

1/1/11

123456

Poly-Vi-Sol #50 ML NDC 76413-337-01

Batch: 123456
Lot: 123456
Exp: 1/1/11
MJN

Federal law prohibits the transfer of this drug to any other person than the patient for whom prescribed.